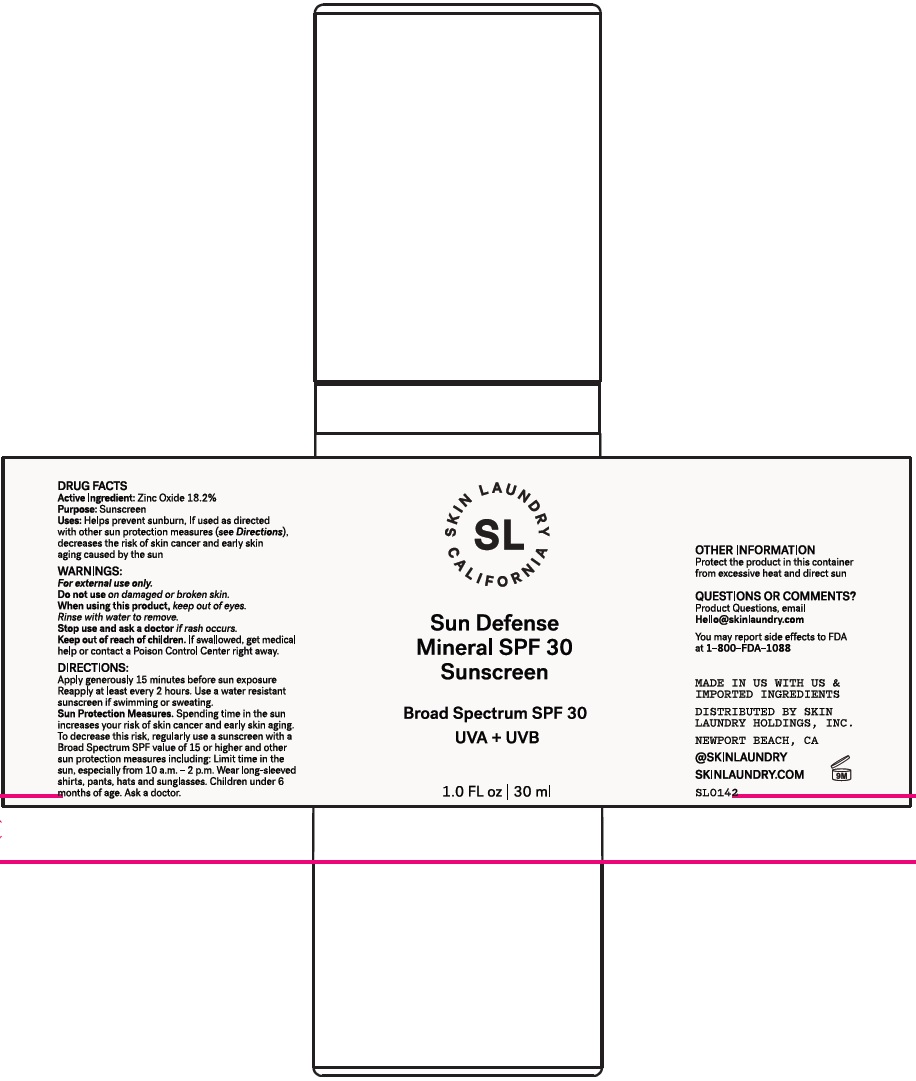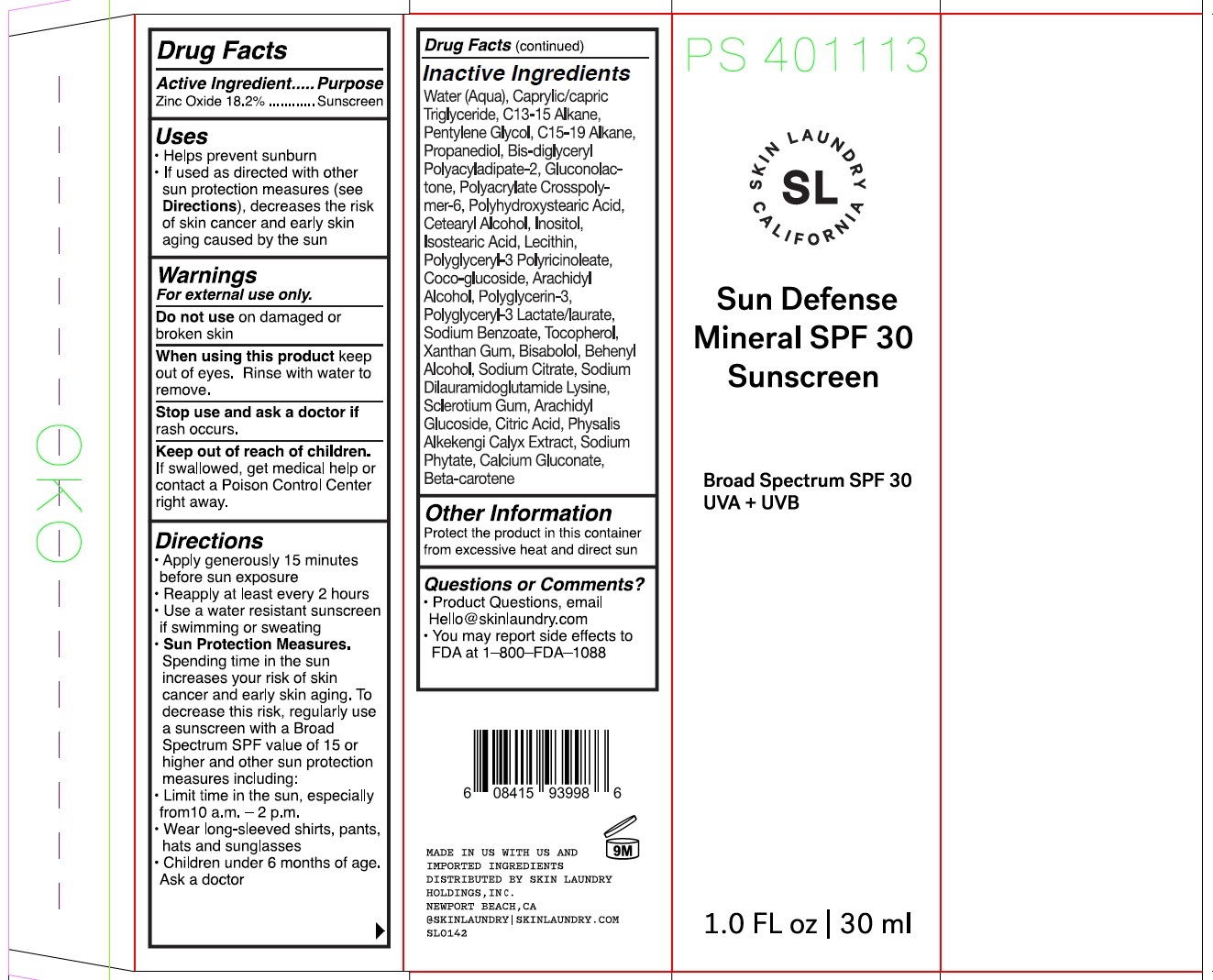 DRUG LABEL: Skin Laundry Sun Defense Mineral SPF 30 Sunscreen Broad Spectrum SPF 30 UVA UVB
NDC: 83727-295 | Form: CREAM
Manufacturer: Skin Laundry Holdings, Inc.
Category: otc | Type: HUMAN OTC DRUG LABEL
Date: 20231006

ACTIVE INGREDIENTS: ZINC OXIDE 182 mg/1 mL
INACTIVE INGREDIENTS: ARACHIDYL GLUCOSIDE; CITRIC ACID MONOHYDRATE; ALKEKENGI OFFICINARUM CALYX; PHYTATE SODIUM; CALCIUM GLUCONATE; BETA CAROTENE; POLYGLYCERIN-3; SODIUM BENZOATE; TOCOPHEROL; XANTHAN GUM; LEVOMENOL; DOCOSANOL; SODIUM CITRATE, UNSPECIFIED FORM; SODIUM DILAURAMIDOGLUTAMIDE LYSINE; WATER; MEDIUM-CHAIN TRIGLYCERIDES; C13-15 ALKANE; PENTYLENE GLYCOL; C15-19 ALKANE; PROPANEDIOL; BIS-DIGLYCERYL POLYACYLADIPATE-2; GLUCONOLACTONE; AMMONIUM ACRYLOYLDIMETHYLTAURATE, DIMETHYLACRYLAMIDE, LAURYL METHACRYLATE AND LAURETH-4 METHACRYLATE COPOLYMER, TRIMETHYLOLPROPANE TRIACRYLATE CROSSLINKED (45000 MPA.S); CETOSTEARYL ALCOHOL; INOSITOL; ISOSTEARIC ACID; COCO GLUCOSIDE; ARACHIDYL ALCOHOL; BETASIZOFIRAN

Skin Laundry. Sun Defense Mineral SPF 30 Sunscreen Broad Spectrum SPF 30 UVA + UVB

Active ingredient

Zinc Oxide 18.2%

Purpose

Sunscreen

Uses

● Helps prevent sunburn ● If used as directed with other sun protection measures (see Directions), decreases the risk of skin cancer and early skin aging caused by the sun.

Warnings

For external use only

Do not use

on damaged or broken skin

When using this product

keep out of eyes. Rinse with water to remove.

Stop use and ask a doctor

if rash occurs.

Keep out of reach of children

If product is swallowed, get medical help or contact a Poison Control Center right away.

Directions

● Apply generously 15 minutes before sun exposure ● Reapply at least every 2 hours ● Use a water resistant sunscreen if swimming or sweating ● Sun Protection Measures. Spending time in the sun increases your risk of skin cancer and early skin ging. To decrease this risk, regularly use a sunscreen with a Broad Spectrum SPF value of 15 or higher and other sun protection measures including: ● Limit time in the sun, especially from 10 a.m. - 2 p.m. ● Wear long-sleeved shirts, pants, hats, and sunglasses ● Children under 6 months: Ask a doctor

Inactive ingredients

Water (Aqua), Caprylic/Capric Triglyceride, C13-15 Alkane, Pentylene Glycol, C15-19 Alkane, Propanediol, Bis-Diglyceryl Polyacyladipate-2, Gluconolactone, Polyacrylate Crosspolymer-6, Polyhydroxystearic Acid, Cetearyl Alcohol, Inositol, Isostearic Acid, Lecithin, Polyglyceryl-3 Polyricinoleate, Coco-Glucoside, Arachidyl Alcohol, Polyglycerin-3, Polyglyceryl-3 Lactate/Laurate, Sodium Benzoate, Tocopherol, Xanthan Gum, Bisabolol, Behenyl Alcohol, Sodium Citrate, Sodium Dilauramidoglutamide Lysine, Sclerotium Gum, Arachidyl Glucoside, Citric Acid, Physalis Alkekengi Calyx Extract, Sodium Phytate, Calcium Gluconate, Beta-Carotene

Other information

Protect the product in this this container from excessive heat and direct sun

Question or comments?

Product Questions, email Hello@skinlaundry.com You may report side effects to FDA at 1-800-FDA-1088